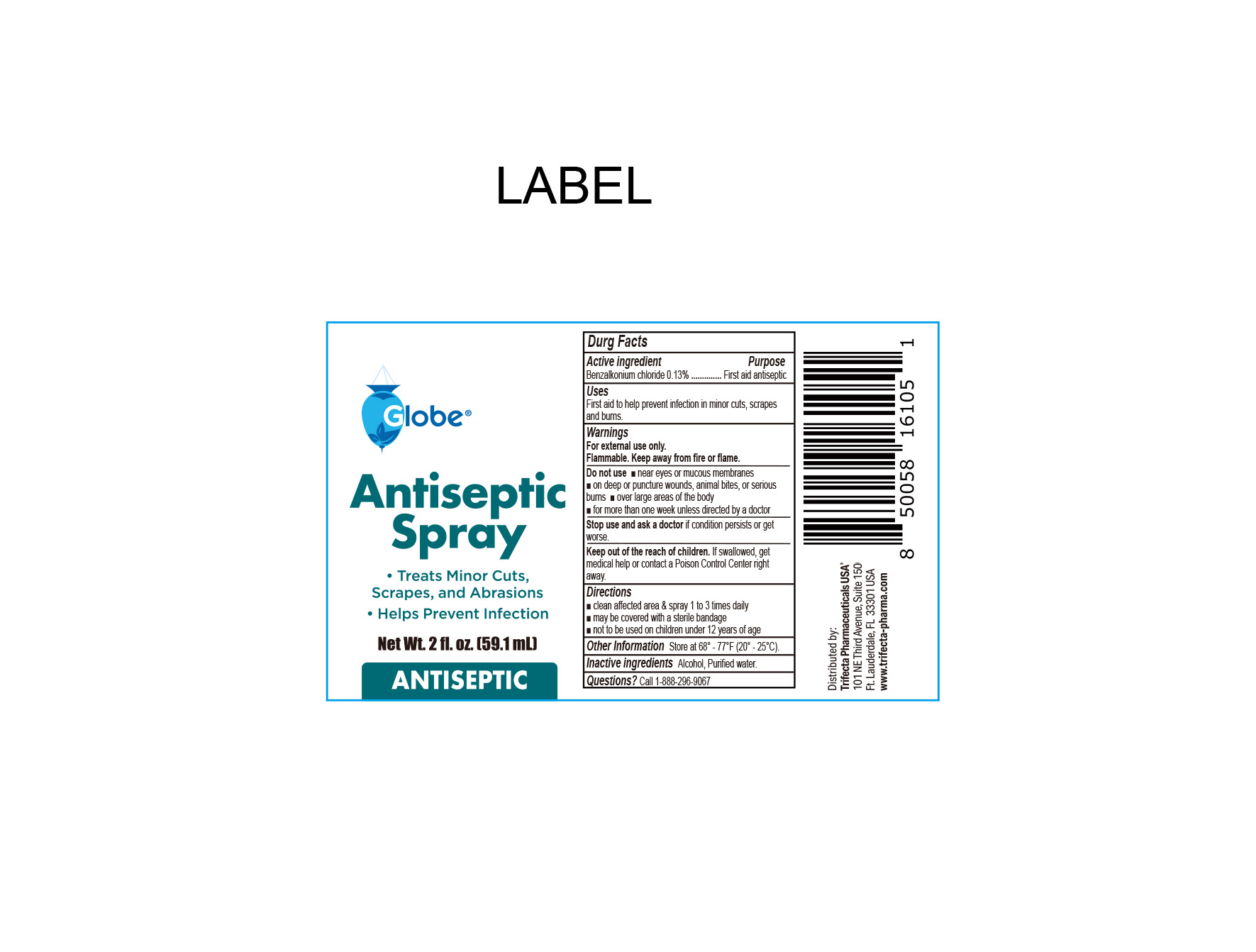 DRUG LABEL: Antiseptic
NDC: 69396-153 | Form: SPRAY
Manufacturer: Trifecta Pharmaceuticals USA, LLC.
Category: otc | Type: HUMAN OTC DRUG LABEL
Date: 20240318

ACTIVE INGREDIENTS: BENZALKONIUM CHLORIDE 1.3 g/1 L
INACTIVE INGREDIENTS: WATER; ALCOHOL

Globe Antiseptic Spray

Active Ingredient

Benzalkonium chloride .13%

Purpose

First Aid Antiseptic

INDICATIONS AND USAGE

First Aid to help prevent infection in minor cuts, scrapes, and burns.

Warnings

For External Use Only

Flammable. Keep away from fire or flame.

Stop use and ask a doctor

- If the condition persists or gets worse.

Keep out of the reach of children

If swallowed, get medical help or contact a Poison Control Center immediately

Directions

- Clean affected area and spray 1 to 3 times daily
- May be covered wiht a sterile bandage
- Not to be used on children under 12 years of age

Do Not Use

- Near eyes or mucous membranes
- on deep or puncture wounds, animal bites, or serious burns
- over large areas of the body
- for more than one week unless directed by a doctor

Other information

- Store at controlled room temperature 68º-77ºF (20º-25ºC)

Inactive Ingredients

Purified water, alcohol

Questions or Comments

Call 1-888-296-9067

Distributed By:

Trifecta Pharmaceuticals USA, LLC.

101 NE Third Avenue, Suite 1500

Ft. Lauderdale, FL. 33301 USA

www.trifecta-pharma.com

SKU: 4069-FBA

Made in China